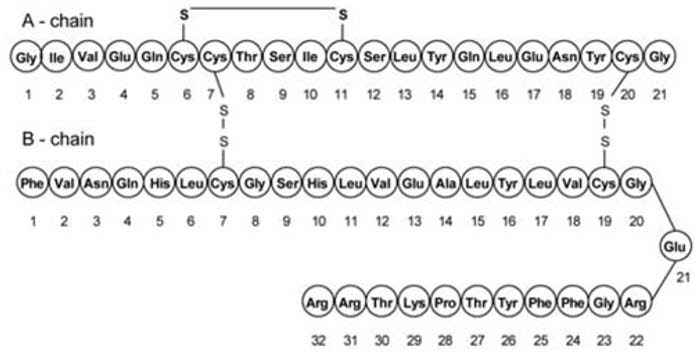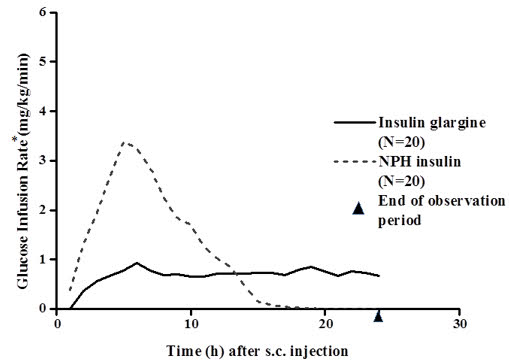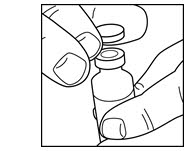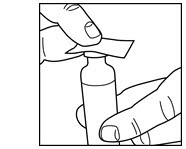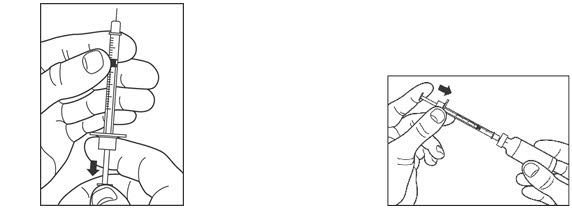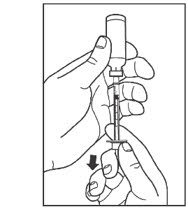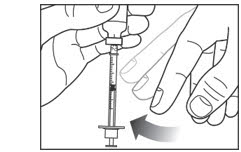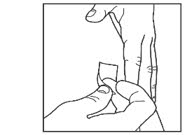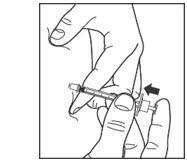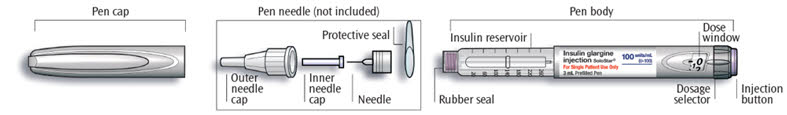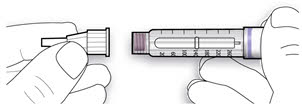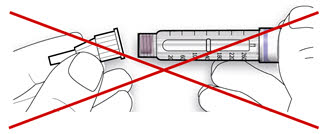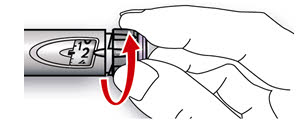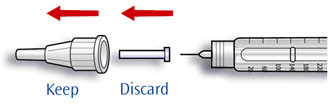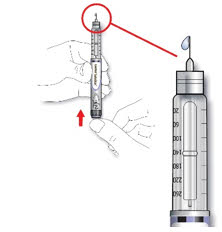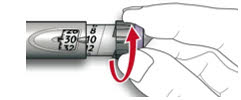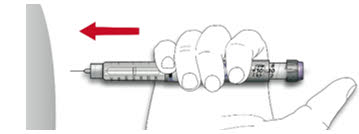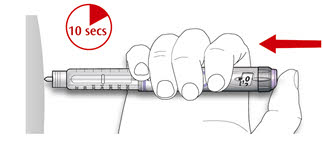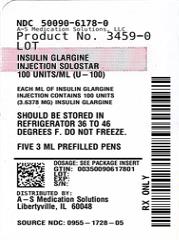 DRUG LABEL: Insulin Glargine Solostar
NDC: 50090-6178 | Form: INJECTION, SOLUTION
Manufacturer: A-S Medication Solutions
Category: prescription | Type: HUMAN PRESCRIPTION DRUG LABEL
Date: 20231101

ACTIVE INGREDIENTS: INSULIN GLARGINE 100 [iU]/1 mL
INACTIVE INGREDIENTS: ZINC 30 ug/1 mL; METACRESOL 2.7 mg/1 mL; GLYCERIN 20 mg/1 mL; WATER; HYDROCHLORIC ACID; SODIUM HYDROXIDE

HIGHLIGHTS OF PRESCRIBING INFORMATION

These highlights do not include all the information needed to use Insulin glargine safely and effectively. See full prescribing information for Insulin glargine.
Insulin glargine injection, for subcutaneous injection
Initial U.S. Approval: 2000

1 INDICATIONS AND USAGE

Insulin glargine is a long-acting human insulin analog indicated to improve glycemic control in adults and pediatric patients with type 1 diabetes mellitus and in adults with type 2 diabetes mellitus. (1)

Limitations of Use

Not recommended for treating diabetic ketoacidosis. (1)

2 DOSAGE AND ADMINISTRATION

- Individualize dosage based on metabolic needs, blood glucose monitoring, glycemic control, type of diabetes, and prior insulin use. (2.1, 2.3, 2.4)
- Administer subcutaneously into the abdominal area, thigh, or deltoid once daily at any time of day, but at the same time every day. (2.1)
- Do not dilute or mix with any other insulin or solution. (2.1)
- Rotate injection sites to reduce risk of lipodystrophy and localized cutaneous amyloidosis. (2.2)
- Closely monitor glucose when changing to Insulin glargine and during initial weeks thereafter. (2.4)

3 DOSAGE FORMS AND STRENGTHS

Injection: 100 units/mL (U-100) available as:

- 10 mL multiple-dose vial (3)
- 3 mL single-patient-use SoloStar prefilled pen (3)

4 CONTRAINDICATIONS

- During episodes of hypoglycemia (4)
- Hypersensitivity to Insulin glargine or one of its excipients (4)

5 WARNINGS AND PRECAUTIONS

- Never share an Insulin glargine SoloStar prefilled pen between patients, even if the needle is changed. (5.1)
- Hyperglycemia or hypoglycemia with changes in insulin regimen: Make changes to a patient's insulin regimen (e.g., insulin strength, manufacturer, type, injection site or method of administration) under close medical supervision with increased frequency of blood glucose monitoring. (5.2)
- Hypoglycemia: May be life-threatening. Increase frequency of glucose monitoring with changes to: insulin dosage, coadministered glucose lowering medications, meal pattern, physical activity; and in patients with renal or hepatic impairment and hypoglycemia unawareness. (5.3, 6.1)
- Medication Errors: Accidental mix-ups between insulin products can occur. Instruct patients to check insulin labels before injection. (5.4, 6.3)
- Hypersensitivity reactions: Severe, life-threatening, generalized allergy, including anaphylaxis, can occur. Discontinue Insulin glargine. Monitor and treat if indicated. (5.5, 6.1)
- Hypokalemia: May be life-threatening. Monitor potassium levels in patients at risk of hypokalemia and treat if indicated. (5.6)
- Fluid retention and heart failure with concomitant use of thiazolidinediones (TZDs): Observe for signs and symptoms of heart failure; consider dosage reduction or discontinuation of TZD if heart failure occurs. (5.7)

6 ADVERSE REACTIONS

Adverse reactions commonly associated with Insulin glargine include hypoglycemia, allergic reactions, injection site reactions, lipodystrophy, pruritus, rash, edema, and weight gain. (6.1)

To report SUSPECTED ADVERSE REACTIONS, contact sanofi-aventis at 1-800-633-1610 or FDA at 1-800-FDA-1088 or www.fda.gov/medwatch.

7 DRUG INTERACTIONS

- Drugs that affect glucose metabolism: Adjustment of insulin dosage may be needed; closely monitor blood glucose. (7)
- Antiadrenergic Drugs (e.g., beta-blockers, clonidine, guanethidine, and reserpine): Signs and symptoms of hypoglycemia may be reduced or absent. (7)

FULL PRESCRIBING INFORMATION

1 INDICATIONS AND USAGE

Insulin glargine is indicated to improve glycemic control in adults and pediatric patients with type 1 diabetes mellitus and in adults with type 2 diabetes mellitus.

Limitations of Use

Insulin glargine is not recommended for the treatment of diabetic ketoacidosis.

2 DOSAGE AND ADMINISTRATION

2.1 Important Administration Instructions

- Administer Insulin glargine subcutaneously once daily at any time of day but at the same time every day.
- Prior to initiation of Insulin glargine, train patients on proper use and injection technique.
- Patient should follow the Instructions for Use to correctly administer Insulin glargine.
- Administer Insulin glargine subcutaneously into the abdominal area, thigh, or deltoid, and rotate injection sites within the same region from one injection to the next to reduce the risk of lipodystrophy and localized cutaneous amyloidosis. Do not inject into areas of lipodystrophy or localized cutaneous amyloidosis [see Warnings and Precautions (5.2), Adverse Reactions (6)].
- During changes to a patient's insulin regimen, increase the frequency of blood glucose monitoring [see Warnings and Precautions (5.2)].
- Visually inspect Insulin glargine vials and SoloStar prefilled pens for particulate matter and discoloration prior to administration. Only use if the solution is clear and colorless with no visible particles.
- The Insulin glargine SoloStar prefilled pen dials in 1-unit increments.
- Use Insulin glargine SoloStar prefilled pen with caution in patients with visual impairment who may rely on audible clicks to dial their dose.
- Refrigerate unused (unopened) Insulin glargine vials and SoloStar® prefilled pens.
- Do not administer intravenously or via an insulin pump.
- Do not dilute or mix Insulin glargine with any other insulin or solution.
- The SoloStar prefilled pen is for single patient use only [see Warnings and Precautions (5.1)].

2.2 General Dosing Instructions

- Individualize and adjust the dosage of Insulin glargine based on the individual's metabolic needs, blood glucose monitoring results and glycemic control goal.
- Dosage adjustments may be needed with changes in physical activity, changes in meal patterns (i.e., macronutrient content or timing of food intake), during acute illness, or changes in renal or hepatic function. Dosage adjustments should only be made under medical supervision with appropriate glucose monitoring [see Warnings and Precautions (5.2)].

2.3 Initiation of Insulin Glargine Therapy

Type 1 Diabetes

- In patients with type 1 diabetes, Insulin glargine must be used concomitantly with short-acting insulin. The recommended starting dose of Insulin glargine in patients with type 1 diabetes should be approximately one-third of the total daily insulin requirements. Short-acting, premeal insulin should be used to satisfy the remainder of the daily insulin requirements.

Type 2 Diabetes

- The recommended starting dose of Insulin glargine in patients with type 2 diabetes who are not currently treated with insulin is 0.2 units/kg or up to 10 units once daily. One may need to adjust the amount and timing of short- or rapid-acting insulins and dosages of any oral antidiabetic drugs.

2.4 Changing to Insulin Glargine from Other Insulin Therapies

- If changing patients from once-daily TOUJEO (insulin glargine) 300 units/mL to once-daily Insulin glargine, the recommended initial Insulin glargine dose is 80% of the TOUJEO dose that is being discontinued. This dose reduction will lower the likelihood of hypoglycemia [see Warnings and Precautions (5.3)].
- If changing from a treatment regimen with an intermediate or long-acting insulin to a regimen with Insulin glargine, a change in the dose of the basal insulin may be required and the amount and timing of the shorter-acting insulins and doses of any oral antidiabetic drugs may need to be adjusted.
- If changing patients from once-daily NPH insulin to once-daily Insulin glargine, the recommended initial Insulin glargine dose is the same as the dose of NPH that is being discontinued.
- If changing patients from twice-daily NPH insulin to once-daily Insulin glargine, the recommended initial Insulin glargine dosage is 80% of the total NPH dose that is being discontinued. This dosage reduction will lower the likelihood of hypoglycemia [see Warnings and Precautions (5.3)].

3 DOSAGE FORMS AND STRENGTHS

Injection: 100 units per mL (U-100) available as:

- 10 mL multiple-dose vial (1,000 units/10 mL)
- 3 mL single-patient-use SoloStar prefilled pen (300 units/3 mL)

4 CONTRAINDICATIONS

Insulin glargine is contraindicated:

- during episodes of hypoglycemia [see Warnings and Precautions (5.3)]
- in patients with hypersensitivity to Insulin glargine or one of its excipients [see Warnings and Precautions (5.5)]

5 WARNINGS AND PRECAUTIONS

5.1 Never Share an Insulin Glargine SoloStar Prefilled Pen, Syringe, or Needle Between Patients

Insulin glargine SoloStar prefilled pens must never be shared between patients, even if the needle is changed. Patients using Insulin glargine vials must never re-use or share needles or syringes with another person. Sharing poses a risk for transmission of blood-borne pathogens.

5.2 Hyperglycemia or Hypoglycemia with Changes in Insulin Regimen

Changes in an insulin regimen (e.g., insulin strength, manufacturer, type, injection site or method of administration) may affect glycemic control and predispose to hypoglycemia [see Warnings and Precautions (5.3)] or hyperglycemia. Repeated insulin injections into areas of lipodystrophy or localized cutaneous amyloidosis have been reported to result in hyperglycemia; and a sudden change in the injection site (to unaffected area) has been reported to result in hypoglycemia [see Adverse Reactions (6)].

Make any changes to a patient's insulin regimen under close medical supervision with increased frequency of blood glucose monitoring. Advise patients who have repeatedly injected into areas of lipodystrophy or localized cutaneous amyloidosis to change the injection site to unaffected areas and closely monitor for hypoglycemia. For patients with type 2 diabetes, dosage adjustments of concomitant oral and antidiabetic products may be needed.

5.3 Hypoglycemia

Hypoglycemia is the most common adverse reaction associated with insulin, including Insulin glargine. Severe hypoglycemia can cause seizures, may be life-threatening or cause death. Hypoglycemia can impair concentration ability and reaction time; this may place an individual and others at risk in situations where these abilities are important (e.g., driving or operating other machinery).

Hypoglycemia can happen suddenly and symptoms may differ in each individual and change over time in the same individual. Symptomatic awareness of hypoglycemia may be less pronounced in patients with longstanding diabetes, in patients with diabetic nerve disease, in patients using medications that block the sympathetic nervous system (e.g., beta-blockers) [see Drug Interactions (7)], or in patients who experience recurrent hypoglycemia.

Risk Factors for Hypoglycemia

The risk of hypoglycemia after an injection is related to the duration of action of the insulin and, in general, is highest when the glucose lowering effect of the insulin is maximal. As with all insulin preparations, the glucose lowering effect time course of Insulin glargine may vary in different individuals or at different times in the same individual and depends on many conditions, including the area of injection as well as the injection site blood supply and temperature [see Clinical Pharmacology (12.2)]. Other factors which may increase the risk of hypoglycemia include changes in meal pattern (e.g., macronutrient content or timing of meals), changes in level of physical activity, or changes to coadministered medication [see Drug Interactions (7)]. Patients with renal or hepatic impairment may be at higher risk of hypoglycemia [see Use in Specific Populations (8.6, 8.7)].

Risk Mitigation Strategies for Hypoglycemia

Patients and caregivers must be educated to recognize and manage hypoglycemia. Self-monitoring of blood glucose plays an essential role in the prevention and management of hypoglycemia. In patients at higher risk for hypoglycemia and patients who have reduced symptomatic awareness of hypoglycemia, increased frequency of blood glucose monitoring is recommended.

The long-acting effect of Insulin glargine may delay recovery from hypoglycemia.

5.4 Medication Errors

Accidental mix-ups among insulin products, particularly between long-acting insulins and rapid-acting insulins, have been reported. To avoid medication errors between Insulin glargine and other insulins, instruct patients to always check the insulin label before each injection [see Adverse Reactions (6.3)].

5.5 Hypersensitivity and Allergic Reactions

Severe, life-threatening, generalized allergy, including anaphylaxis, can occur with insulin products, including Insulin glargine. If hypersensitivity reactions occur, discontinue Insulin glargine; treat per standard of care and monitor until symptoms and signs resolve [see Adverse Reactions (6.1)]. Insulin glargine is contraindicated in patients who have had hypersensitivity reactions to insulin glargine or one of the excipients [see Contraindications (4)].

5.6 Hypokalemia

All insulin products, including Insulin glargine, cause a shift in potassium from the extracellular to intracellular space, possibly leading to hypokalemia. Untreated hypokalemia may cause respiratory paralysis, ventricular arrhythmia, and death. Monitor potassium levels in patients at risk for hypokalemia, if indicated (e.g., patients using potassium-lowering medications, patients taking medications sensitive to serum potassium concentrations).

5.7 Fluid Retention and Heart Failure with Concomitant Use of PPAR-gamma Agonists

Thiazolidinediones (TZDs), which are peroxisome proliferator-activated receptor (PPAR)-gamma agonists, can cause dose-related fluid retention, particularly when used in combination with insulin. Fluid retention may lead to or exacerbate heart failure. Patients treated with insulin, including Insulin glargine, and a PPAR-gamma agonist should be observed for signs and symptoms of heart failure. If heart failure develops, it should be managed according to current standards of care, and discontinuation or dose reduction of the PPAR-gamma agonist must be considered.

6 ADVERSE REACTIONS

The following adverse reactions are discussed elsewhere:

- Hypoglycemia [see Warnings and Precautions (5.3)]
- Hypersensitivity and allergic reactions [see Warnings and Precautions (5.5)]
- Hypokalemia [see Warnings and Precautions (5.6)]

6.1 Clinical Trials Experience

Because clinical trials are conducted under widely varying conditions, adverse reaction rates observed in clinical trials of a drug cannot be directly compared to rates in the clinical trial of another drug and may not reflect the rates observed in practice.

The data in Table 1 reflect the exposure of 2327 patients with type 1 diabetes to Insulin glargine or NPH. The type 1 diabetes population had the following characteristics: Mean age was 38.5 years. Fifty-four percent were male, 96.9% were Caucasian, 1.8% were Black or African American and 2.7% were Hispanic. The mean BMI was 25.1 kg/m^2.

The data in Table 2 reflect the exposure of 1563 patients with type 2 diabetes to Insulin glargine or NPH. The type 2 diabetes population had the following characteristics: Mean age was 59.3 years. Fifty-eight percent were male, 86.7% were Caucasian, 7.8% were Black or African American and 9% were Hispanic. The mean BMI was 29.2 kg/m^2.

The frequencies of adverse events during Insulin glargine clinical trials in patients with type 1 diabetes mellitus and type 2 diabetes mellitus are listed in the tables below.

Table 1: Adverse Events in Pooled Clinical Trials up to 28 Weeks Duration in Adults with Type 1 Diabetes (adverse events with frequency ≥5%)
 | Insulin glargine, % (n=1257) | NPH, % (n=1070)
Upper respiratory tract infection | 22.4 | 23.1
Infection [Body system not specified] | 9.4 | 10.3
Accidental injury | 5.7 | 6.4
Headache | 5.5 | 4.7

Table 2: Adverse Events in Pooled Clinical Trials up to 1 Year Duration in Adults with Type 2 Diabetes (adverse events with frequency ≥5%)
 | Insulin glargine, % (n=849) | NPH, % (n=714)
Upper respiratory tract infection | 11.4 | 13.3
Infection [Body system not specified] | 10.4 | 11.6
Retinal vascular disorder | 5.8 | 7.4

Table 3: Adverse Events in a 5-Year Trial of Adults with Type 2 Diabetes (adverse events with frequency ≥10%)
 | Insulin glargine, % (n=514) | NPH, % (n=503)
Upper respiratory tract infection | 29.0 | 33.6
Edema peripheral | 20.0 | 22.7
Hypertension | 19.6 | 18.9
Influenza | 18.7 | 19.5
Sinusitis | 18.5 | 17.9
Cataract | 18.1 | 15.9
Bronchitis | 15.2 | 14.1
Arthralgia | 14.2 | 16.1
Pain in extremity | 13.0 | 13.1
Back pain | 12.8 | 12.3
Cough | 12.1 | 7.4
Urinary tract infection | 10.7 | 10.1
Diarrhea | 10.7 | 10.3
Depression | 10.5 | 9.7
Headache | 10.3 | 9.3

Table 4: Adverse Events in a 28-Week Clinical Trial of Children and Adolescents with Type 1 Diabetes (adverse events with frequency ≥5%)
 | Insulin glargine, % (n=174) | NPH, % (n=175)
Infection [Body system not specified] | 13.8 | 17.7
Upper respiratory tract infection | 13.8 | 16.0
Pharyngitis | 7.5 | 8.6
Rhinitis | 5.2 | 5.1

Severe Hypoglycemia

Hypoglycemia is the most commonly observed adverse reaction in patients using insulin, including Insulin glargine [see Warnings and Precautions (5.3)]. Tables 5, 6, and 7 summarize the incidence of severe hypoglycemia in the Insulin glargine individual clinical trials. Severe symptomatic hypoglycemia was defined as an event with symptoms consistent with hypoglycemia requiring the assistance of another person and associated with either a blood glucose below 50 mg/dL (≤56 mg/dL in the 5-year trial and ≤36 mg/dL in the ORIGIN trial) or prompt recovery after oral carbohydrate, intravenous glucose, or glucagon administration.

Percentages of Insulin glargine–treated adult patients experiencing severe symptomatic hypoglycemia in the Insulin glargine clinical trials [see Clinical Studies (14)] were comparable to percentages of NPH-treated patients for all treatment regimens (see Tables 5 and 6). In the pediatric phase 3 clinical trial, children and adolescents with type 1 diabetes had a higher incidence of severe symptomatic hypoglycemia in the two treatment groups compared to the adult trials with type 1 diabetes.

Table 5: Severe Symptomatic Hypoglycemia in Patients with Type 1 Diabetes
 | Study A Type 1 Diabetes Adults 28 weeks In combination with regular insulin |  | Study B Type 1 Diabetes Adults 28 weeks In combination with regular insulin |  | Study C Type 1 Diabetes Adults 16 weeks In combination with insulin lispro |  | Study D Type 1 Diabetes Pediatrics 26 weeks In combination with regular insulin
 | Insulin glargine N=292 | NPH N=293 | Insulin glargine N=264 | NPH N=270 | Insulin glargine N=310 | NPH N=309 | Insulin glargine N=174 | NPH N=175
Percent of patients | 10.6 | 15.0 | 8.7 | 10.4 | 6.5 | 5.2 | 23.0 | 28.6

Table 6: Severe Symptomatic Hypoglycemia in Patients with Type 2 Diabetes
 | Study E Type 2 Diabetes Adults 52 weeks In combination with oral agents |  | Study F Type 2 Diabetes Adults 28 weeks In combination with regular insulin |  | Study G Type 2 Diabetes Adults 5 years In combination with regular insulin
 | Insulin glargine N=289 | NPH N=281 | Insulin glargine N=259 | NPH N=259 | Insulin glargine N=513 | NPH N=504
Percent of patients | 1.7 | 1.1 | 0.4 | 2.3 | 7.8 | 11.9

Table 7 displays the proportion of patients experiencing severe symptomatic hypoglycemia in the Insulin glargine and Standard Care groups in the ORIGIN Trial [see Clinical Studies (14)].

Table 7: Severe Symptomatic Hypoglycemia in the ORIGIN Trial
 | ORIGIN Trial Median duration of follow-up: 6.2 years
 | Insulin glargine N=6231 | Standard Care N=6273
Percent of patients | 5.6 | 1.8

Peripheral Edema

Some patients taking Insulin glargine have experienced sodium retention and edema, particularly if previously poor metabolic control is improved by intensified insulin therapy.

Lipodystrophy

Administration of insulin subcutaneously, including Insulin glargine, has resulted in lipoatrophy (depression in the skin) or lipohypertrophy (enlargement or thickening of tissue) in some patients [see Dosage and Administration (2.2)].

Insulin Initiation and Intensification of Glucose Control

Intensification or rapid improvement in glucose control has been associated with a transitory, reversible ophthalmologic refraction disorder, worsening of diabetic retinopathy, and acute painful peripheral neuropathy. However, long-term glycemic control decreases the risk of diabetic retinopathy and neuropathy.

Weight Gain

Weight gain has occurred with some insulin therapies including Insulin glargine and has been attributed to the anabolic effects of insulin and the decrease in glucosuria.

Allergic Reactions

Local allergy

As with any insulin therapy, patients taking Insulin glargine may experience injection site reactions, including redness, pain, itching, urticaria, edema, and inflammation. In clinical studies in adult patients, there was a higher incidence of treatment-emergent injection site pain in Insulin glargine–treated patients (2.7%) compared to NPH insulin-treated patients (0.7%). The reports of pain at the injection site did not result in discontinuation of therapy.

Systemic allergy

Severe, life-threatening, generalized allergy, including anaphylaxis, generalized skin reactions, angioedema, bronchospasm, hypotension, and shock may occur with any insulin, including Insulin glargine and may be life threatening.

6.2 Immunogenicity

As with all therapeutic proteins, there is potential for immunogenicity. All insulin products can elicit the formation of insulin antibodies. The presence of such insulin antibodies may increase or decrease the efficacy of insulin and may require adjustment of the insulin dose. In phase 3 clinical trials of Insulin glargine, increases in titers of antibodies to insulin were observed in NPH insulin and Insulin glargine treatment groups with similar incidences.

6.3 Postmarketing Experience

The following adverse reactions have been identified during postapproval use of Insulin glargine. Because these reactions are reported voluntarily from a population of uncertain size, it is not always possible to reliably estimate their frequency or establish a causal relationship to drug exposure.

Medication errors have been reported in which other insulins, particularly rapid-acting insulins, have been accidentally administered instead of Insulin glargine [see Patient Counseling Information (17)]. To avoid medication errors between Insulin glargine and other insulins, patients should be instructed to always verify the insulin label before each injection.

Localized cutaneous amyloidosis at the injection site has occurred. Hyperglycemia has been reported with repeated insulin injections into areas of localized cutaneous amyloidosis; hypoglycemia has been reported with a sudden change to an unaffected injection site.

7 DRUG INTERACTIONS

Table 8 includes clinically significant drug interactions with Insulin glargine.

Table 8: Clinically Significant Drug Interactions with Insulin Glargine
Drugs that May Increase the Risk of Hypoglycemia
Drugs: | Antidiabetic agents, ACE inhibitors, angiotensin II receptor blocking agents, disopyramide, fibrates, fluoxetine, monoamine oxidase inhibitors, pentoxifylline, pramlintide, salicylates, somatostatin analogs (e.g., octreotide), and sulfonamide antibiotics.
Intervention: | Dose reductions and increased frequency of glucose monitoring may be required when Insulin glargine is coadministered with these drugs.
Drugs that May Decrease the Blood Glucose Lowering Effect of Insulin Glargine
Drugs: | Atypical antipsychotics (e.g., olanzapine and clozapine), corticosteroids, danazol, diuretics, estrogens, glucagon, isoniazid, niacin, oral contraceptives, phenothiazines, progestogens (e.g., in oral contraceptives), protease inhibitors, somatropin, sympathomimetic agents (e.g., albuterol, epinephrine, terbutaline), and thyroid hormones.
Intervention: | Dose increases and increased frequency of glucose monitoring may be required when Insulin glargine is coadministered with these drugs.
Drugs that May Increase or Decrease the Blood Glucose Lowering Effect of Insulin Glargine
Drugs: | Alcohol, beta-blockers, clonidine, and lithium salts. Pentamidine may cause hypoglycemia, which may sometimes be followed by hyperglycemia.
Intervention: | Dose adjustment and increased frequency of glucose monitoring may be required when Insulin glargine is coadministered with these drugs.
Drugs that May Blunt Signs and Symptoms of Hypoglycemia
Drugs: | Beta-blockers, clonidine, guanethidine, and reserpine.
Intervention: | Increased frequency of glucose monitoring may be required when Insulin glargine is coadministered with these drugs.

8 USE IN SPECIFIC POPULATIONS

8.1 Pregnancy

Risk Summary

Published studies with use of insulin glargine during pregnancy have not reported a clear association with insulin glargine and adverse developmental outcomes [see Data]. There are risks to the mother and fetus associated with poorly controlled diabetes in pregnancy [see Clinical Considerations].

Rats and rabbits were exposed to insulin glargine in animal reproduction studies during organogenesis, respectively 50 times and 10 times the human subcutaneous dose of 0.2 units/kg/day. Overall, the effects of insulin glargine did not generally differ from those observed with regular human insulin [see Data].

The estimated background risk of major birth defects is 6% to 10% in women with pregestational diabetes with an HbA1c >7 and has been reported to be as high as 20% to 25% in women with a HbA1c >10. The estimated background risk of miscarriage for the indicated population is unknown. In the U.S. general population, the estimated background risk of major birth defects and miscarriage in clinically recognized pregnancies is 2% to 4% and 15% to 20%, respectively.

Clinical Considerations

Disease-associated maternal and/or embryo-fetal risk

Poorly controlled diabetes in pregnancy increases the maternal risk for diabetic ketoacidosis, preeclampsia, spontaneous abortions, preterm delivery, and delivery complications. Poorly controlled diabetes increases the fetal risk for major birth defects, stillbirth, and macrosomia-related morbidity.

Data

Human data

Published data do not report a clear association with insulin glargine and major birth defects, miscarriage, or adverse maternal or fetal outcomes when insulin glargine is used during pregnancy. However, these studies cannot definitely establish the absence of any risk because of methodological limitations including small sample size and some lacking comparator groups.

Animal data

Subcutaneous reproduction and teratology studies have been performed with insulin glargine and regular human insulin in rats and Himalayan rabbits. Insulin glargine was given to female rats before mating, during mating, and throughout pregnancy at doses up to 0.36 mg/kg/day, which is approximately 50 times the recommended human subcutaneous starting dose of 0.2 units/kg/day (0.007 mg/kg/day), on a mg/kg basis. In rabbits, doses of 0.072 mg/kg/day, which is approximately 10 times the recommended human subcutaneous starting dose of 0.2 units/kg/day on a mg/kg basis, were administered during organogenesis. The effects of insulin glargine did not generally differ from those observed with regular human insulin in rats or rabbits. However, in rabbits, five fetuses from two litters of the high-dose group exhibited dilation of the cerebral ventricles. Fertility and early embryonic development appeared normal.

8.2 Lactation

Risk Summary

There are either no or only limited data on the presence of insulin glargine in human milk, the effects on breastfed infant, or the effects on milk production. Endogenous insulin is present in human milk. The developmental and health benefits of breastfeeding should be considered along with the mother's clinical need for insulin glargine, and any potential adverse effects on the breastfed child from insulin glargine or from the underlying maternal condition.

8.4 Pediatric Use

The safety and effectiveness of Insulin glargine have been established in pediatric patients (age 6 to 15 years) with type 1 diabetes [see Clinical Studies (14.2)]. The safety and effectiveness of Insulin glargine in pediatric patients younger than 6 years of age with type 1 diabetes and pediatric patients with type 2 diabetes have not been established.

The dosage recommendation when changing to Insulin glargine in pediatric patients (age 6 to 15 years) with type 1 diabetes is the same as that described for adults [see Dosage and Administration (2.2, 2.4), Clinical Studies (14)]. As in adults, the dosage of Insulin glargine must be individualized in pediatric patients (age 6 to 15 years) with type 1 diabetes based on metabolic needs and frequent monitoring of blood glucose.

In the pediatric clinical trial, pediatric patients (age 6 to 15 years) with type 1 diabetes had a higher incidence of severe symptomatic hypoglycemia compared to the adults in trials with type 1 diabetes [see Adverse Reactions (6.1)].

8.5 Geriatric Use

Of the total number of subjects in controlled clinical studies of patients with type 1 and type 2 diabetes who were treated with Insulin glargine, 15% were ≥65 years of age and 2% were ≥75 years of age. The only difference in safety or effectiveness in the subpopulation of patients ≥65 years of age compared to the entire study population was a higher incidence of cardiovascular events typically seen in an older population in the Insulin glargine and NPH treatment groups.

Nevertheless, caution should be exercised when Insulin glargine is administered to geriatric patients. In elderly patients with diabetes, the initial dosing, dose increments, and maintenance dosage should be conservative to avoid hypoglycemic reactions. Hypoglycemia may be difficult to recognize in the elderly.

8.6 Hepatic Impairment

The effect of hepatic impairment on the pharmacokinetics of Insulin glargine has not been studied. Frequent glucose monitoring and dose adjustment may be necessary for Insulin glargine in patients with hepatic impairment [see Warnings and Precautions (5.3)].

8.7 Renal Impairment

The effect of renal impairment on the pharmacokinetics of Insulin glargine has not been studied. Some studies with human insulin have shown increased circulating levels of insulin in patients with renal failure. Frequent glucose monitoring and dose adjustment may be necessary for Insulin glargine in patients with renal impairment [see Warnings and Precautions (5.3)].

8.8 Obesity

In controlled clinical trials, subgroup analyses based on BMI did not show differences in safety and efficacy between Insulin glargine and NPH.

10 OVERDOSAGE

Excess insulin administration may cause hypoglycemia and hypokalemia [see Warnings and Precautions (5.3, 5.6)]. Mild episodes of hypoglycemia can usually be treated with oral carbohydrates. Adjustments in drug dosage, meal patterns, or exercise may be needed.

More severe episodes of hypoglycemia with coma, seizure, or neurologic impairment may be treated with intramuscular/subcutaneous glucagon or concentrated intravenous glucose. After apparent clinical recovery from hypoglycemia, continued observation and additional carbohydrate intake may be necessary to avoid recurrence of hypoglycemia. Hypokalemia must be corrected appropriately.

11 DESCRIPTION

Insulin glargine (insulin glargine injection) is a sterile solution of insulin glargine for subcutaneous use. Insulin glargine is a recombinant human insulin analog that is a long-acting, parenteral blood-glucose-lowering agent [see Clinical Pharmacology (12)]. Insulin glargine has low aqueous solubility at neutral pH. At pH 4 insulin glargine is completely soluble. After injection into the subcutaneous tissue, the acidic solution is neutralized, leading to formation of microprecipitates from which small amounts of insulin glargine are slowly released, resulting in a relatively constant concentration/time profile over 24 hours with no pronounced peak. This profile allows once-daily dosing as a basal insulin. Insulin glargine is produced by recombinant DNA technology utilizing a non-pathogenic laboratory strain of Escherichia coli (K12) as the production organism. Insulin glargine differs from human insulin in that the amino acid asparagine at position A21 is replaced by glycine and two arginines are added to the C-terminus of the B-chain. Chemically, insulin glargine is 21A-Gly-30Ba-L-Arg-30Bb-L-Arg-human insulin and has the empirical formula C267H404N72O78S6 and a molecular weight of 6063. Insulin glargine has the following structural formula:

Insulin glargine consists of insulin glargine dissolved in a clear aqueous fluid. Each milliliter of insulin glargine injection contains 100 units (3.6378 mg) insulin glargine.

The 10 mL vial presentation contains the following inactive ingredients per mL: 30 mcg zinc, 2.7 mg m-cresol, 20 mg glycerol 85%, 20 mcg polysorbate 20, and water for injection.

The 3 mL prefilled pen presentation contains the following inactive ingredients per mL: 30 mcg zinc, 2.7 mg m-cresol, 20 mg glycerol 85%, and water for injection.

The pH is adjusted by addition of aqueous solutions of hydrochloric acid and sodium hydroxide. Insulin glargine has a pH of approximately 4.

12 CLINICAL PHARMACOLOGY

12.1 Mechanism of Action

The primary activity of insulin, including insulin glargine, is regulation of glucose metabolism. Insulin and its analogs lower blood glucose by stimulating peripheral glucose uptake, especially by skeletal muscle and fat, and by inhibiting hepatic glucose production. Insulin inhibits lipolysis and proteolysis, and enhances protein synthesis.

12.2 Pharmacodynamics

In clinical studies, the glucose-lowering effect on a molar basis (i.e., when given at the same doses) of intravenous insulin glargine is approximately the same as that for human insulin. Figure 1 shows results from a study in patients with type 1 diabetes conducted for a maximum of 24 hours after the injection. The median time between injection and the end of pharmacological effect was 14.5 hours (range: 9.5 to 19.3 hours) for NPH insulin, and 24 hours (range: 10.8 to >24.0 hours) (24 hours was the end of the observation period) for insulin glargine.

Figure 1: Activity Profile in Patients with Type 1 Diabetes

* Determined as amount of glucose infused to maintain constant plasma glucose levels

The duration of action after abdominal, deltoid, or thigh subcutaneous administration was similar. The time course of action of insulins, including Insulin glargine, may vary between individuals and within the same individual.

12.3 Pharmacokinetics

Absorption and Bioavailability

After subcutaneous injection of Insulin glargine in healthy subjects and in patients with diabetes, the insulin serum concentrations indicated a slower, more prolonged absorption and a relatively constant concentration/time profile over 24 hours with no pronounced peak in comparison to NPH insulin.

Metabolism and Elimination

A metabolism study in humans indicates that insulin glargine is partly metabolized at the carboxyl terminus of the B chain in the subcutaneous depot to form two active metabolites with in vitro activity similar to that of human insulin, M1 (21A-Gly-insulin) and M2 (21A-Gly-des-30B-Thr-insulin). Unchanged drug and these degradation products are also present in the circulation.

Special Populations

Age, race, and gender

Effect of age, race, and gender on the pharmacokinetics of Insulin glargine has not been evaluated. However, in controlled clinical trials in adults (n=3890) and a controlled clinical trial in pediatric patients (n=349), subgroup analyses based on age, race, and gender did not show differences in safety and efficacy between Insulin glargine and NPH insulin [see Clinical Studies (14)].

Obesity

Effect of Body Mass Index (BMI) on the pharmacokinetics of Insulin glargine has not been evaluated.

13 NONCLINICAL TOXICOLOGY

13.1 Carcinogenesis, Mutagenesis, Impairment of Fertility

In mice and rats, standard two-year carcinogenicity studies with insulin glargine were performed at doses up to 0.455 mg/kg, which was for the rat approximately 65 times the recommended human subcutaneous starting dose of 0.2 units/kg/day (0.007 mg/kg/day) on a mg/kg basis. Histiocytomas were found at injection sites in male rats and mice in acid vehicle containing groups and are considered a response to chronic tissue irritation and inflammation in rodents. These tumors were not found in female animals, in saline control, or insulin comparator groups using a different vehicle.

Insulin glargine was not mutagenic in tests for detection of gene mutations in bacteria and mammalian cells (Ames and HGPRT-test) and in tests for detection of chromosomal aberrations (cytogenetics in vitro in V79 cells and in vivo in Chinese hamsters).

In a combined fertility and prenatal and postnatal study in male and female rats at subcutaneous doses up to 0.36 mg/kg/day, which was approximately 50 times the recommended human subcutaneous starting dose of 0.2 units/kg/day (0.007 mg/kg/day) maternal toxicity due to dose-dependent hypoglycemia, including some deaths, was observed. Consequently, a reduction of the rearing rate occurred in the high-dose group only. Similar effects were observed with NPH insulin.

14 CLINICAL STUDIES

14.1 Overview of Clinical Studies

The safety and effectiveness of Insulin glargine given once-daily at bedtime was compared to that of once-daily and twice-daily NPH insulin in open-label, randomized, active-controlled, parallel studies of 2,327 adult patients and 349 pediatric patients with type 1 diabetes mellitus and 1,563 adult patients with type 2 diabetes mellitus (see Tables 9–11). In general, the reduction in glycated hemoglobin (HbA1c) with Insulin glargine was similar to that with NPH insulin.

14.2 Clinical Studies in Adult and Pediatric Patients with Type 1 Diabetes

In two clinical studies (Studies A and B), patients with type 1 diabetes (Study A n=585, Study B n=534) were randomized to 28 weeks of basal-bolus treatment with Insulin glargine or NPH insulin. Regular human insulin was administered before each meal. Insulin glargine was administered at bedtime. NPH insulin was administered either as once daily at bedtime or in the morning and at bedtime when used twice daily.

In Study A, the average age was 39.2 years. The majority of patients were White (99%) and 55.7% were male. The mean BMI was approximately 24.9 kg/m^2. The mean duration of diabetes was 15.5 years.

In Study B, the average age was 38.5 years. The majority of patients were White (95.3%) and 50.6% were male. The mean BMI was approximately 25.8 kg/m^2. The mean duration of diabetes was 17.4 years.

In another clinical study (Study C), patients with type 1 diabetes (n=619) were randomized to 16 weeks of basal-bolus treatment with Insulin glargine or NPH insulin. Insulin lispro was used before each meal. Insulin glargine was administered once daily at bedtime and NPH insulin was administered once or twice daily. The average age was 39.2 years. The majority of patients were White (96.9%) and 50.6% were male. The mean BMI was approximately 25.6 kg/m^2. The mean duration of diabetes was 18.5 years.

In these 3 studies, Insulin glargine and NPH insulin had similar effects on HbA1c (Table 9) with a similar overall rate of severe symptomatic hypoglycemia [see Adverse Reactions (6.1)].

Table 9: Type 1 Diabetes Mellitus – Adult
 | Study A |  | Study B |  | Study C
Treatment duration | 28 weeks |  | 28 weeks |  | 16 weeks
Treatment in combination with | Regular insulin |  | Regular insulin |  | Insulin lispro
 | Insulin glargine | NPH | Insulin glargine | NPH | Insulin glargine | NPH
Number of subjects treated | 292 | 293 | 264 | 270 | 310 | 309
HbA1c
Baseline HbA1c | 8.0 | 8.0 | 7.7 | 7.7 | 7.6 | 7.7
Adjusted mean change at trial end | +0.2 | +0.1 | -0.2 | -0.2 | -0.1 | -0.1
Treatment Difference (95% CI) | +0.1 (0.0; +0.2) |  | +0.1 (-0.1; +0.2) |  | 0.0 (-0.1; +0.1)
Basal insulin dose
Baseline mean | 21 | 23 | 29 | 29 | 28 | 28
Mean change from baseline | -2 | 0 | -4 | +2 | -5 | +1
Total insulin dose
Baseline mean | 48 | 52 | 50 | 51 | 50 | 50
Mean change from baseline | -1 | 0 | 0 | +4 | -3 | 0
Fasting blood glucose (mg/dL)
Baseline mean | 167 | 166 | 166 | 175 | 175 | 173
Adj. mean change from baseline | -21 | -16 | -20 | -17 | -29 | -12
Body weight (kg)
Baseline mean | 73.2 | 74.8 | 75.5 | 75.0 | 74.8 | 75.6
Mean change from baseline | 0.1 | -0.0 | 0.7 | 1.0 | 0.1 | 0.5

Type 1 Diabetes – Pediatric (see Table 10)

In a randomized, controlled clinical study (Study D), pediatric patients (age range 6 to 15 years) with type 1 diabetes (n=349) were treated for 28 weeks with a basal-bolus insulin regimen where regular human insulin was used before each meal. Insulin glargine was administered once daily at bedtime and NPH insulin was administered once or twice daily. The average age was 11.7 years. The majority of patients were White (96.8%) and 51.9% were male. The mean BMI was approximately 18.9 kg/m^2. The mean duration of diabetes was 4.8 years. Similar effects on HbA1c (Table 10) were observed in both treatment groups [see Adverse Reactions (6.1)].

Table 10: Type 1 Diabetes Mellitus – Pediatric
 | Study D
Treatment duration | 28 weeks
Treatment in combination with | Regular insulin
 | Insulin glargine + Regular Insulin | NPH + Regular Insulin
Number of subjects treated | 174 | 175
HbA1c
Baseline mean | 8.5 | 8.8
Change from baseline (adjusted mean) | +0.3 | +0.3
Difference from NPH (adjusted mean) | 0.0
(95% CI) | (-0.2; +0.3)
Basal insulin dose
Baseline mean | 19 | 19
Mean change from baseline | -1 | +2
Total insulin dose
Baseline mean | 43 | 43
Mean change from baseline | +2 | +3
Fasting blood glucose (mg/dL)
Baseline mean | 194 | 191
Mean change from baseline | -23 | -12
Body weight (kg)
Baseline mean | 45.5 | 44.6
Mean change from baseline | 2.2 | 2.5

14.3 Clinical Studies in Adults with Type 2 Diabetes

In a randomized, controlled clinical study (Study E) (n=570), Insulin glargine was evaluated for 52 weeks in combination with oral antidiabetic medications (a sulfonylurea, metformin, acarbose, or combinations of these drugs). The average age was 59.5 years. The majority of patients were White (92.8%) and 53.7% were male. The mean BMI was approximately 29.1 kg/m^2. The mean duration of diabetes was 10.3 years. Insulin glargine administered once daily at bedtime was as effective as NPH insulin administered once daily at bedtime in reducing HbA1c and fasting glucose (Table 11). The rate of severe symptomatic hypoglycemia was similar in Insulin glargine and NPH insulin treated patients [see Adverse Reactions (6.1)].

In a randomized, controlled clinical study (Study F), in patients with type 2 diabetes not using oral antidiabetic medications (n=518), a basal-bolus regimen of Insulin glargine once daily at bedtime or NPH insulin administered once or twice daily was evaluated for 28 weeks. Regular human insulin was used before meals, as needed. The average age was 59.3 years. The majority of patients were White (80.7%) and 60% were male. The mean BMI was approximately 30.5 kg/m^2. The mean duration of diabetes was 13.7 years. Insulin glargine had similar effectiveness as either once- or twice-daily NPH insulin in reducing HbA1c and fasting glucose (Table 11) with a similar incidence of hypoglycemia [see Adverse Reactions (6.1)].

In a randomized, controlled clinical study (Study G), patients with type 2 diabetes were randomized to 5 years of treatment with once-daily Insulin glargine or twice-daily NPH insulin. For patients not previously treated with insulin, the starting dose of Insulin glargine or NPH insulin was 10 units daily. Patients who were already treated with NPH insulin either continued on the same total daily NPH insulin dose or started Insulin glargine at a dose that was 80% of the total previous NPH insulin dose. The primary endpoint for this study was a comparison of the progression of diabetic retinopathy by 3 or more steps on the Early Treatment Diabetic Retinopathy Study (ETDRS) scale. HbA1c change from baseline was a secondary endpoint. Similar glycemic control in the 2 treatment groups was desired in order to not confound the interpretation of the retinal data. Patients or study personnel used an algorithm to adjust the Insulin glargine and NPH insulin doses to a target fasting plasma glucose ≤100 mg/dL. After the Insulin glargine or NPH insulin dose was adjusted, other antidiabetic agents, including premeal insulin were to be adjusted or added. The average age was 55.1 years. The majority of patients were White (85.3%) and 53.9% were male. The mean BMI was approximately 34.3 kg/m^2. The mean duration of diabetes was 10.8 years. The Insulin glargine group had a smaller mean reduction from baseline in HbA1c compared to the NPH insulin group, which may be explained by the lower daily basal insulin doses in the Insulin glargine group (Table 11). The incidences of severe symptomatic hypoglycemia were similar between groups [see Adverse Reactions (6.1)].

Table 11: Type 2 Diabetes Mellitus – Adult
 | Study E |  | Study F |  | Study G
Treatment duration | 52 weeks |  | 28 weeks |  | 5 years
Treatment in combination with | Oral agents |  | Regular insulin |  | Regular insulin
 | Insulin glargine | NPH | Insulin glargine | NPH | Insulin glargine | NPH
Number of subjects treated | 289 | 281 | 259 | 259 | 513 | 504
HbA1c
Baseline mean | 9.0 | 8.9 | 8.6 | 8.5 | 8.4 | 8.3
Adjusted mean change from baseline | -0.5 | -0.4 | -0.4 | -0.6 | -0.6 | -0.8
Insulin glargine – NPH | -0.1 |  | +0.2 |  | +0.2
95% CI for Treatment difference | (-0.3; +0.1) |  | (0.0; +0.4) |  | (+0.1; +0.4)
Basal insulin dose [In Study G, the baseline dose of basal or total insulin was the first available on-treatment dose prescribed during the study (on visit month 1.5).]
Baseline mean | 14 | 15 | 44.1 | 45.5 | 39 | 44
Mean change from baseline | +12 | +9 | -1 | +7 | +23 | +30
Total insulin dose
Baseline mean | 14 | 15 | 64 | 67 | 48 | 53
Mean change from baseline | +12 | +9 | +10 | +13 | +41 | +40
Fasting blood glucose (mg/dL)
Baseline mean | 179 | 180 | 164 | 166 | 190 | 180
Adj. mean change from baseline | -49 | -46 | -24 | -22 | -45 | -44
Body weight (kg)
Baseline mean | 83.5 | 82.1 | 89.6 | 90.7 | 100 | 99
Adj. mean change from baseline | 2.0 | 1.9 | 0.4 | 1.4 | 3.7 | 4.8

Insulin Glargine Timing of Daily Dosing (see Table 12)

The safety and efficacy of Insulin glargine administered pre-breakfast, pre-dinner, or at bedtime were evaluated in a randomized, controlled clinical study in patients with type 1 diabetes (Study H, n=378). Patients were also treated with insulin lispro at mealtime. The average age was 40.9 years. All patients were White (100%) and 53.7% were male. The mean BMI was approximately 25.3 kg/m^2. The mean duration of diabetes was 17.3 years. Insulin glargine administered at different times of the day resulted in similar reductions in HbA1c compared to that with bedtime administration (see Table 12). In these patients, data are available from 8-point home glucose monitoring. The maximum mean blood glucose was observed just prior to injection of Insulin glargine regardless of time of administration.

In this study, 5% of patients in the Insulin glargine–breakfast arm discontinued treatment because of lack of efficacy. No patients in the other two arms discontinued for this reason. The safety and efficacy of Insulin glargine administered pre-breakfast or at bedtime were also evaluated in a randomized, active-controlled clinical study (Study I, n=697) in patients with type 2 diabetes not adequately controlled on oral antidiabetic therapy. All patients in this study also received glimepiride 3 mg daily. The average age was 60.8 years. The majority of patients were White (96.6%) and 53.7% were male. The mean BMI was approximately 28.7 kg/m^2. The mean duration of diabetes was 10.1 years. Insulin glargine given before breakfast was at least as effective in lowering HbA1c as Insulin glargine given at bedtime or NPH insulin given at bedtime (see Table 12).

Table 12: Insulin Glargine Timing of Daily Dosing in Type 1 (Study H) and Type 2 (Study I) Diabetes Mellitus
 | Study H |  |  | Study I
Treatment duration | 24 weeks |  |  | 24 weeks
Treatment in combination with | Insulin lispro |  |  | Glimepiride
 | Insulin glargine Breakfast | Insulin glargine Dinner | Insulin glargine Bedtime | Insulin glargine Breakfast | Insulin glargine Bedtime | NPH Bedtime
Number of subjects treated [Intent-to-treat] | 112 | 124 | 128 | 234 | 226 | 227
HbA1c
Baseline mean | 7.6 | 7.5 | 7.6 | 9.1 | 9.1 | 9.1
Mean change from baseline | -0.2 | -0.1 | 0.0 | -1.3 | -1.0 | -0.8
Basal insulin dose (U)
Baseline mean | 22 | 23 | 21 | 19 | 20 | 19
Mean change from baseline | 5 | 2 | 2 | 11 | 18 | 18
Total insulin dose (U) |  |  |  | NA [Not applicable] | NA | NA
Baseline mean | 52 | 52 | 49 | – | – | –
Mean change from baseline | 2 | 3 | 2 | – | – | –
Body weight (kg)
Baseline mean | 77.1 | 77.8 | 74.5 | 80.7 | 82 | 81
Mean change from baseline | 0.7 | 0.1 | 0.4 | 3.9 | 3.7 | 2.9

Five-Year Trial Evaluating the Progression of Retinopathy

Retinopathy was evaluated in the Insulin glargine clinical studies by analysis of reported retinal adverse events and fundus photography. The numbers of retinal adverse events reported for Insulin glargine and NPH insulin treatment groups were similar for patients with type 1 and type 2 diabetes.

Insulin glargine was compared to NPH insulin in a 5-year randomized clinical trial that evaluated the progression of retinopathy as assessed with fundus photography using a grading protocol derived from the Early Treatment Diabetic Retinopathy Scale (ETDRS). Patients had type 2 diabetes (mean age 55 years) with no (86%) or mild (14%) retinopathy at baseline. Mean baseline HbA1c was 8.4%. The primary outcome was progression by 3 or more steps on the ETDRS scale at study endpoint. Patients with prespecified postbaseline eye procedures (pan-retinal photocoagulation for proliferative or severe nonproliferative diabetic retinopathy, local photocoagulation for new vessels, and vitrectomy for diabetic retinopathy) were also considered as 3-step progressors regardless of actual change in ETDRS score from baseline. Retinopathy graders were blinded to treatment group assignment. The results for the primary endpoint are shown in Table 13 for both the per-protocol and intent-to-treat populations, and indicate similarity of Insulin glargine to NPH in the progression of diabetic retinopathy as assessed by this outcome.

Table 13: Number (%) of Patients with 3 or More Step Progression on ETDRS Scale at Endpoint
 | Insulin glargine (%) | NPH (%) | Difference [Difference = Insulin glargine – NPH] , [Using a generalized linear model (SAS GENMOD) with treatment and baseline HbA1c strata (cutoff 9.0%) as the classified independent variables, and with binomial distribution and identity link function] (SE) | 95% CI for difference
Per-protocol | 53/374 (14.2%) | 57/363 (15.7%) | -2.0% (2.6%) | -7.0% to +3.1%
Intent-to-Treat | 63/502 (12.5%) | 71/487 (14.6%) | -2.1% (2.1%) | -6.3% to +2.1%

The Origin Study

The Outcome Reduction with Initial Glargine Intervention trial (i.e., ORIGIN) was an open-label, randomized, 2-by-2, factorial design study. One intervention in ORIGIN compared the effect of Insulin glargine to standard care on major adverse cardiovascular outcomes in 12,537 participants ≥50 years of age with abnormal glucose levels (i.e., impaired fasting glucose [IFG] and/or impaired glucose tolerance [IGT]) or early type 2 diabetes mellitus and established cardiovascular (i.e., CV) disease or CV risk factors at baseline.

The objective of the trial was to demonstrate that Insulin glargine use could significantly lower the risk of major cardiovascular outcomes compared to standard care. Two coprimary composite cardiovascular endpoints were used in ORIGIN. The first coprimary endpoint was the time to first occurrence of a major adverse cardiovascular event defined as the composite of CV death, nonfatal myocardial infarction, and nonfatal stroke. The second coprimary endpoint was the time to the first occurrence of CV death or nonfatal myocardial infarction or nonfatal stroke or revascularization procedure or hospitalization for heart failure.

Participants were randomized to either Insulin glargine (N=6264) titrated to a goal fasting plasma glucose of ≤95 mg/dL or to standard care (N=6273). Anthropometric and disease characteristics were balanced at baseline. The mean age was 64 years and 8% of participants were 75 years of age or older. The majority of participants were male (65%). Fifty nine percent were Caucasian, 25% were Latin, 10% were Asian and 3% were Black. The median baseline BMI was 29 kg/m^2. Approximately 12% of participants had abnormal glucose levels (IGT and/or IFG) at baseline and 88% had type 2 diabetes. For patients with type 2 diabetes, 59% were treated with a single oral antidiabetic drug, 23% had known diabetes but were on no antidiabetic drug and 6% were newly diagnosed during the screening procedure. The mean HbA1c (SD) at baseline was 6.5% (1.0). Fifty-nine percent of participants had had a prior cardiovascular event and 39% had documented coronary artery disease or other cardiovascular risk factors.

Vital status was available for 99.9% and 99.8% of participants randomized to Insulin glargine and standard care respectively at end of trial. The median duration of follow-up was 6.2 years (range: 8 days to 7.9 years). The mean HbA1c (SD) at the end of the trial was 6.5% (1.1) and 6.8% (1.2) in the Insulin glargine and standard care group respectively. The median dose of Insulin glargine at end of trial was 0.45 U/kg. Eighty-one percent of patients randomized to Insulin glargine were using Insulin glargine at end of the study. The mean change in body weight from baseline to the last treatment visit was 2.2 kg greater in the Insulin glargine group than in the standard care group.

Overall, the incidence of major adverse cardiovascular outcomes was similar between groups (see Table 14). All-cause mortality was also similar between groups.

Table 14: Cardiovascular Outcomes in ORIGIN – Time to First Event Analyses
 | Insulin glargine N=6264 | Standard Care N=6273 | Insulin glargine vs Standard Care
 | n (Events per 100 PY) | n (Events per 100 PY) | Hazard Ratio (95% CI)
Coprimary endpoints
CV death, nonfatal myocardial infarction, or nonfatal stroke | 1041 (2.9) | 1013 (2.9) | 1.02 (0.94, 1.11)
CV death, nonfatal myocardial infarction, nonfatal stroke, hospitalization for heart failure or revascularization procedure | 1792 (5.5) | 1727 (5.3) | 1.04 (0.97, 1.11)
Components of coprimary endpoints
CV death | 580 | 576 | 1.00 (0.89, 1.13)
Myocardial Infarction (fatal or nonfatal) | 336 | 326 | 1.03 (0.88, 1.19)
Stroke (fatal or nonfatal) | 331 | 319 | 1.03 (0.89, 1.21)
Revascularizations | 908 | 860 | 1.06 (0.96, 1.16)
Hospitalization for heart failure | 310 | 343 | 0.90 (0.77, 1.05)

In the ORIGIN trial, the overall incidence of cancer (all types combined) or death from cancer (Table 15) was similar between treatment groups.

Table 15: Cancer Outcomes in ORIGIN – Time to First Event Analyses
 | Insulin glargine N=6264 | Standard Care N=6273 | Insulin glargine vs Standard Care
 | n (Events per 100 PY) | n (Events per 100 PY) | Hazard Ratio (95% CI)
Cancer endpoints
Any cancer event (new or recurrent) | 559 (1.56) | 561 (1.56) | 0.99 (0.88, 1.11)
New cancer events | 524 (1.46) | 535 (1.49) | 0.96 (0.85, 1.09)
Death due to Cancer | 189 (0.51) | 201 (0.54) | 0.94 (0.77, 1.15)

16 HOW SUPPLIED/STORAGE AND HANDLING

Product: 50090-6178

NDC: 50090-6178-0 3 mL in a SYRINGE / 5 in a CARTON

17 PATIENT COUNSELING INFORMATION

Advise the patient to read the FDA-approved patient labeling (Patient Information and Instructions for Use).

Never Share an Insulin Glargine SoloStar Prefilled Pen or Syringe Between Patients

Advise patients that they must never share an Insulin glargine SoloStar prefilled pen with another person, even if the needle is changed. Advise patients using Insulin glargine vials not to re-use or share needles or syringes with another person. Sharing carries a risk for transmission of blood-borne pathogens [see Warnings and Precautions (5.1)].

Hyperglycemia or Hypoglycemia

Inform patients that hypoglycemia is the most common adverse reaction with insulin. Inform patients of the symptoms of hypoglycemia. Inform patients that the ability to concentrate and react may be impaired as a result of hypoglycemia. This may present a risk in situations where these abilities are especially important, such as driving or operating other machinery. Advise patients who have frequent hypoglycemia or reduced or absent warning signs of hypoglycemia to use caution when driving or operating machinery [see Warnings and Precautions (5.3)].

Advise patients that changes in insulin regimen can predispose to hyperglycemia or hypoglycemia and that changes in insulin regimen should be made under close medical supervision [see Warnings and Precautions (5.2)].

Medications Errors

Instruct patients to always check the insulin label before each injection [see Warnings and Precautions (5.4)].

Administration

Advise patients that Insulin glargine must NOT be diluted or mixed with any other insulin or solution and that Insulin glargine must only be used if the solution is clear and colorless with no particles visible [see Dosage and Administration (2)].

Winthrop U.S.,
a business of sanofi-aventis U.S. LLC
Bridgewater, NJ 08807
A SANOFI COMPANY

©2021 sanofi-aventis U.S. LLC

TOUJEO and SoloStar are registered trademarks of sanofi-aventis U.S. LLC.

Patient Information
Insulin glargine (IN-su-lin-GLAR-gine)
(insulin glargine injection) for subcutaneous use, 100 Units/mL (U-100)

Do not share your syringes with other people, even if the needle has been changed. You may give other people a serious infection, or get a serious infection from them.
What is Insulin glargine?
Insulin glargine is a long-acting man-made-insulin used to control high blood sugar in adults with diabetes mellitus.

- Insulin glargine is not for use to treat diabetic ketoacidosis.
- It is not known if Insulin glargine is safe and effective in children less than 6 years of age with type 1 diabetes.
- It is not known if Insulin glargine is safe and effective in children with type 2 diabetes.

Who should not use Insulin glargine?
Do not use Insulin glargine if you:

- are having an episode of low blood sugar (hypoglycemia).
- have an allergy to insulin glargine or any of the ingredients in Insulin glargine. See the end of this Patient Information leaflet for a complete list of ingredients in Insulin glargine.

What should I tell my healthcare provider before using Insulin glargine?
Before using Insulin glargine, tell your healthcare provider about all your medical conditions including if you:

- have liver or kidney problems.
- take other medicines, especially ones called TZDs (thiazolidinediones).
- have heart failure or other heart problems. If you have heart failure, it may get worse while you take TZDs with Insulin glargine.
- are pregnant, planning to become pregnant, or are breastfeeding. It is not known if Insulin glargine may harm your unborn baby or breastfeeding baby.

Tell your healthcare provider about all the medicines you take including prescription and over-the-counter medicines, vitamins, and herbal supplements.
Before you start using Insulin glargine, talk to your healthcare provider about low blood sugar and how to manage it.

How should I use Insulin glargine?

- Read the detailed Instructions for Use that come with your Insulin glargine insulin.
- Use Insulin glargine exactly as your healthcare provider tells you to. Your healthcare provider should tell you how much Insulin glargine to use and when to use it.
- Know the amount of Insulin glargine you use. Do not change the amount of Insulin glargine you use unless your healthcare provider tells you to.
- Check your insulin label each time you give your injection to make sure you are using the correct insulin.
- Do not re-use needles. Always use a new needle for each injection. Re-use of needles increases your risk of having blocked needles, which may cause you to get the wrong dose of Insulin glargine. Using a new needle for each injection lowers your risk of getting an infection.
- You may take Insulin glargine at any time during the day but you must take it at the same time every day.
- Only use Insulin glargine that is clear and colorless. If your Insulin glargine is cloudy or slightly colored, return it to your pharmacy for a replacement.
- Insulin glargine is injected under the skin (subcutaneously) of your upper legs (thighs), upper arms, or stomach area (abdomen).
- Do not use Insulin glargine in an insulin pump or inject Insulin glargine into your vein (intravenously).
- Change (rotate) injection sites within the area you chose with each dose to reduce your risk of getting lipodystrophy (pits in skin or thickened skin) and localized cutaneous amyloidosis (skin with lumps) at the injection sites.
  - Do not use the exact same spot for each injection.
  - Do not inject where the skin has pits, is thickened, or has lumps.
  - Do not inject where the skin is tender, bruised, scaly or hard, or into scars or damaged skin.
- Do not mix Insulin glargine with any other type of insulin or liquid medicine.
- Check your blood sugar levels. Ask your healthcare provider what your blood sugar should be and when you should check your blood sugar levels.

Keep Insulin glargine and all medicines out of the reach of children.

Your dose of Insulin glargine may need to change because of:

- a change in level of physical activity or exercise, weight gain or loss, increased stress, illness, change in diet, or because of the medicines you take.

What should I avoid while using Insulin glargine?
While using Insulin glargine do not:

- drive or operate heavy machinery, until you know how Insulin glargine affects you.
- drink alcohol or use over-the-counter medicines that contain alcohol.

What are the possible side effects of Insulin glargine and other insulins?
Insulin glargine may cause serious side effects that can lead to death, including:

- low blood sugar (hypoglycemia). Signs and symptoms that may indicate low blood sugar include:
  - dizziness or light-headedness, sweating, confusion, headache, blurred vision, slurred speech, shakiness, fast heartbeat, anxiety, irritability or mood change, hunger.
- severe allergic reaction (whole body reaction). Get medical help right away if you have any of these signs or symptoms of a severe allergic reaction:
  - a rash over your whole body, trouble breathing, a fast heartbeat, or sweating.
- low potassium in your blood (hypokalemia).
- Heart failure. Taking certain diabetes pills called TZDs (thiazolidinediones) with Insulin glargine may cause heart failure in some people. This can happen even if you have never had heart failure or heart problems before. If you already have heart failure it may get worse while you take TZDs with Insulin glargine. Your healthcare provider should monitor you closely while you are taking TZDs with Insulin glargine. Tell your healthcare provider if you have any new or worse symptoms of heart failure including:
  - shortness of breath, swelling of your ankles or feet, sudden weight gain.
  Treatment with TZDs and Insulin glargine may need to be changed or stopped by your healthcare provider if you have new or worse heart failure.

Get emergency medical help if you have:

- trouble breathing; shortness of breath; fast heartbeat; swelling of your face, tongue, or throat; sweating; extreme drowsiness; dizziness; confusion.

The most common side effects of Insulin glargine include:

- low blood sugar (hypoglycemia); weight gain; allergic reactions, including reactions at your injection site; skin thickening or pits at the injection site (lipodystrophy).

These are not all the possible side effects of Insulin glargine. Call your doctor for medical advice about side effects. You may report side effects to FDA at 1-800-FDA-1088.

General information about the safe and effective use of Insulin glargine.
Medicines are sometimes prescribed for purposes other than those listed in a Patient Information leaflet. Do not use Insulin glargine for a condition for which it was not prescribed. Do not give Insulin glargine to other people, even if they have the same symptoms that you have. It may harm them.
This Patient Information leaflet summarizes the most important information about Insulin glargine. If you would like more information, talk with your healthcare provider. You can ask your pharmacist or healthcare provider for information about Insulin glargine that is written for healthcare professionals. For more information, go to www.winthropus.com or call 1-800-633-1610.

What are the ingredients in Insulin glargine?

- Active ingredient: insulin glargine
- 10 mL vial inactive ingredients: zinc, m-cresol, glycerol, polysorbate, and water for injection

Manufactured by: Winthrop U.S., a business of sanofi-aventis U.S. LLC, Bridgewater, NJ 08807

This Patient Information has been approved by the U.S. Food and Drug Administration

Revised: December 2020

Instructions for Use

Insulin glargine (IN-su-lin-GLAR-gine)
injection for subcutaneous use
10 mL Vial (100 Units/mL, U-100)

Read the Instructions for Use before you start taking Insulin glargine and each time you get a new Insulin glargine vial. There may be new information. This information does not take the place of talking to your healthcare provider about your medical condition or your treatment.

Do not share your Insulin glargine syringes with other people even if the needle has been changed. You may give other people a serious infection, or get a serious infection from them.

Supplies needed to give your injection:

- an Insulin glargine 10 mL vial
- a U-100 insulin syringe and needle
- 2 alcohol swabs
- 1 sharps container for throwing away used needles and syringes. See "Disposing of used needles and syringes" at the end of these instructions.

Preparing your Insulin glargine dose:

- Wash your hands with soap and water or with alcohol.
- Check the Insulin glargine label to make sure you are taking the right type of insulin. This is especially important if you use more than 1 type of insulin.
- Check the insulin to make sure it is clear and colorless. Do not use Insulin glargine if it is colored or cloudy, or if you see particles in the solution.
- Do not use Insulin glargine after the expiration date stamped on the label or 28 days after you first use it.
- Always use a syringe that is marked for U-100 insulin. If you use a syringe other than a U-100 insulin syringe, you may get the wrong dose of insulin.
- Always use a new syringe or needle for each injection. Do not re-use or share your syringes or needles with other people. You may give other people a serious infection or get a serious infection from them.

Step 1:

If you are using a new vial, remove the protective cap. Do not remove the stopper.

Step 2:

Wipe the top of the vial with an alcohol swab. You do not have to shake the vial of Insulin glargine before use.

Step 3:

Draw air into the syringe equal to your insulin dose. Put the needle through the rubber top of the vial and push the plunger to inject the air into the vial.

Step 4:

Leave the syringe in the vial and turn both upside down. Hold the syringe and vial firmly in one hand. Make sure the tip of the needle is in the insulin. With your free hand, pull the plunger to withdraw the correct dose into the syringe.

Step 5:

Before you take the needle out of the vial, check the syringe for air bubbles. If bubbles are in the syringe, hold the syringe straight up and tap the side of the syringe until the bubbles float to the top. Push the bubbles out with the plunger and draw insulin back in until you have the correct dose.

Step 6:

Remove the needle from the vial. Do not let the needle touch anything. You are now ready to inject.

Giving your Insulin glargine injection:

- Inject your insulin exactly as your healthcare provider has shown you.
- Inject your insulin under the skin (subcutaneously) of your upper legs (thighs), upper arms, or stomach area (abdomen).
- Change (rotate) your injection sites within the area you choose for each dose to reduce your risk of getting lipodystrophy (pits in the skin or thickened skin) and localized cutaneous amyloidosis (skin with lumps) at the injection sites.
- Do not inject where the skin has pits, is thickened, or has lumps.
- Do not inject where the skin is tender, bruised, scaly or hard, or into scars or damaged skin.

Step 7:

Choosing your injection site: Insulin glargine is injected under the skin (subcutaneously) of your upper arm, thigh, or stomach area (abdomen). Wipe the skin with an alcohol swab to clean the injection site. Let the injection site dry before you inject your dose.

Step 8:

- Pinch the skin.
- Insert the needle in the way your healthcare provider showed you.
- Release the skin.
- Slowly push in the plunger of the syringe all the way, making sure you have injected all the insulin.
- Leave the needle in the skin for about 10 seconds.

Step 9:

- Pull the needle straight out of your skin.
- Gently press the injection site for several seconds. Do not rub the area.
- Do not recap the used needle. Recapping the needle can lead to a needle stick injury.

Disposing of used needles and syringes:

- Put your used needles and syringes in a FDA-cleared sharps disposal container right away after use. Do not throw away (dispose of) loose needles and syringes in your household trash.
- If you do not have a FDA-cleared sharps container, you may use a household container that is:
  - made of a heavy-duty plastic,
  - can be closed with a tight-fitting, puncture-resistant lid, without sharps being able to come out,
  - upright and stable during use,
  - leak resistant, and
  - properly labeled to warn of hazardous waste inside the container.
- When your sharps disposal container is almost full, you will need to follow your community guidelines for the right way to dispose of your sharps disposal container. There may be state or local laws about how you should throw away used needles and syringes. For more information about safe sharps disposal, and for specific information about sharps disposal in the state that you live in, go to the FDA's website at: http://www.fda.gov/safesharpsdisposal.
- Do not dispose of your used sharps disposal container in your household trash unless your community guidelines permit this. Do not recycle your used sharps disposal container.

How should I store Insulin glargine?

- Store unused Insulin glargine vials in the refrigerator between 36°F to 46°F (2°C to 8°C).
- Store in-use (opened) Insulin glargine vials in a refrigerator or at room temperature below 86°F (30°C).
- Do not freeze Insulin glargine.
- Keep Insulin glargine out of direct heat and light.
- If a vial has been frozen or overheated, throw it away.
- The Insulin glargine vials you are using should be thrown away after 28 days, even if it still has insulin left in it.

This Instructions for Use has been approved by the U.S. Food and Drug Administration.

Revised: December 2020

Winthrop U.S.,
a business of sanofi-aventis U.S. LLC
Bridgewater, NJ 08807
A SANOFI COMPANY

©2020 sanofi-aventis U.S. LLC

INSTRUCTIONS FOR USE

Patient Information
Insulin glargine (IN-su-lin-GLAR-gine)
(insulin glargine injection) for subcutaneous use, 100 Units/mL (U-100)

Do not share your Insulin glargine SoloStar® pen with other people, even if the needle has been changed. You may give other people a serious infection, or get a serious infection from them.
What is Insulin glargine?
Insulin glargine is a long-acting man-made insulin used to control high blood sugar in adults with diabetes mellitus.

- Insulin glargine is not for use to treat diabetic ketoacidosis.
- It is not known if Insulin glargine is safe and effective in children less than 6 years of age with type 1 diabetes.
- It is not known if Insulin glargine is safe and effective in children with type 2 diabetes.

Who should not use Insulin glargine?
Do not use Insulin glargine if you:

- are having an episode of low blood sugar (hypoglycemia).
- have an allergy to insulin glargine or any of the ingredients in Insulin glargine. See the end of this Patient Information leaflet for a complete list of ingredients in Insulin glargine.

What should I tell my healthcare provider before using Insulin glargine?
Before using Insulin glargine, tell your healthcare provider about all your medical conditions including if you:

- have liver or kidney problems.
- take other medicines, especially ones called TZDs (thiazolidinediones).
- have heart failure or other heart problems. If you have heart failure, it may get worse while you take TZDs with Insulin glargine.
- are pregnant, planning to become pregnant, or are breastfeeding. It is not known if Insulin glargine may harm your unborn baby or breastfeeding baby.

Tell your healthcare provider about all the medicines you take including prescription and over-the-counter medicines, vitamins, and herbal supplements.
Before you start using Insulin glargine, talk to your healthcare provider about low blood sugar and how to manage it.

How should I use Insulin glargine?

- Read the detailed Instructions for Use that come with your Insulin glargine SoloStar single-patient-use prefilled pen.
- Use Insulin glargine exactly as your healthcare provider tells you to. Your healthcare provider should tell you how much Insulin glargine to use and when to use it.
- Know the amount of Insulin glargine you use. Do not change the amount of Insulin glargine you use unless your healthcare provider tells you to.
- Check your insulin label each time you give your injection to make sure you are using the correct insulin.
- Insulin glargine comes in a SoloStar single-patient-use prefilled pen that you must use to give your Insulin glargine. The dose counter on your pen shows your dose of Insulin glargine. Do not make any dose changes unless your healthcare provider tells you to.
- Do not use a syringe to remove Insulin glargine from your SoloStar disposable prefilled pen.
- Do not re-use needles. Always use a new needle for each injection. Re-use of needles increases your risk of having blocked needles, which may cause you to get the wrong dose of Insulin glargine. Using a new needle for each injection lowers your risk of getting an infection. If your needle is blocked, follow the instructions in Step 3 of the Instructions for Use.
- You may take Insulin glargine at any time during the day but you must take it at the same time every day.
- Insulin glargine is injected under the skin (subcutaneously) of your upper legs (thighs), upper arms, or stomach area (abdomen).
- Do not use Insulin glargine in an insulin pump or inject Insulin glargine into your vein (intravenously).
- Change (rotate) your injection sites within area you chose with each dose to reduce your risk of getting lipodystrophy (pits in skin or thickened skin) and localized cutaneous amyloidosis (skin with lumps) at the injection sites.
  - Do not use the exact same spot for each injection.
  - Do not inject where the skin has pits, is thickened, or has lumps.
  - Do not inject where skin is tender, bruised, scaly or hard, or into scars or damaged skin.
- Do not mix Insulin glargine with any other type of insulin or liquid medicine.
- Check your blood sugar levels. Ask your healthcare provider what your blood sugar should be and when you should check your blood sugar levels.

Keep Insulin glargine and all medicines out of the reach of children.

Your dose of Insulin glargine may need to change because of:

- a change in level of physical activity or exercise, weight gain or loss, increased stress, illness, change in diet, or because of the medicines you take.

What should I avoid while using Insulin glargine?
While using Insulin glargine do not:

- drive or operate heavy machinery, until you know how Insulin glargine affects you.
- drink alcohol or use over-the-counter medicines that contain alcohol.

What are the possible side effects of Insulin glargine and other insulins?
Insulin glargine may cause serious side effects that can lead to death, including:

- low blood sugar (hypoglycemia). Signs and symptoms that may indicate low blood sugar include:
  - dizziness or light-headedness, sweating, confusion, headache, blurred vision, slurred speech, shakiness, fast heartbeat, anxiety, irritability or mood change, hunger.
- severe allergic reaction (whole body reaction). Get medical help right away if you have any of these signs or symptoms of a severe allergic reaction:
  - a rash over your whole body, trouble breathing, a fast heartbeat, or sweating.
- low potassium in your blood (hypokalemia).
- Heart failure. Taking certain diabetes pills called TZDs (thiazolidinediones) with Insulin glargine may cause heart failure in some people. This can happen even if you have never had heart failure or heart problems before. If you already have heart failure it may get worse while you take TZDs with Insulin glargine. Your healthcare provider should monitor you closely while you are taking TZDs with Insulin glargine. Tell your healthcare provider if you have any new or worse symptoms of heart failure including:
  - shortness of breath, swelling of your ankles or feet, sudden weight gain.
  Treatment with TZDs and Insulin glargine may need to be changed or stopped by your healthcare provider if you have new or worse heart failure.

Get emergency medical help if you have:

- trouble breathing; shortness of breath; fast heartbeat; swelling of your face, tongue, or throat; sweating; extreme drowsiness; dizziness; confusion.

The most common side effects of Insulin glargine include:

- low blood sugar (hypoglycemia); weight gain; allergic reactions, including reactions at your injection site; skin thickening or pits at the injection site (lipodystrophy).

These are not all the possible side effects of Insulin glargine. Call your doctor for medical advice about side effects. You may report side effects to FDA at 1-800-FDA-1088.

General information about the safe and effective use of Insulin glargine.
Medicines are sometimes prescribed for purposes other than those listed in a Patient Information leaflet. Do not use Insulin glargine for a condition for which it was not prescribed. Do not give Insulin glargine to other people, even if they have the same symptoms that you have. It may harm them.
This Patient Information leaflet summarizes the most important information about Insulin glargine. If you would like more information, talk with your healthcare provider. You can ask your healthcare provider or pharmacist for information about Insulin glargine that is written for healthcare professionals. For more information about Insulin glargine call 1-800-633-1610 or go to the website www.winthropus.com.

What are the ingredients in Insulin glargine?

- Active ingredient: insulin glargine
- 3 mL SoloStar prefilled pen inactive ingredients: zinc, m-cresol, glycerol, and water for injection

Hydrochloric acid and sodium hydroxide may be added to adjust the pH.

Manufactured by: Winthrop U.S., a business of sanofi-aventis U.S., LLC Bridgewater, NJ 08807

This Patient Information has been approved by the U.S. Food and Drug Administration.

Revised: December 2020

Instructions for Use

Insulin Glargine® SOLOSTAR® Single-Patient-Use Prefilled Pen
(insulin glargine injection)

Your healthcare professional has decided that SoloStar is right for you. Talk with your healthcare professional about proper injection technique before using SoloStar.

Read these instructions carefully before using your SoloStar. If you are not able to follow all the instructions completely on your own, use SoloStar only if you have help from a person who is able to follow the instructions.

Do not share your Insulin glargine SoloStar pen with other people, even if the needle has been changed. You may give other people a serious infection, or get a serious infection from them.

People who are blind or have vision problems should not use Insulin glargine SoloStar single-patient-use prefilled pen without help from a person trained to use Insulin glargine SoloStar single-patient-use prefilled pen.

Follow these instructions completely each time you use SoloStar to ensure that you get an accurate dose. If you do not follow these instructions you may get too much or too little insulin, which may affect your blood glucose.

SoloStar is a disposable pen for the injection of insulin. Each SoloStar contains in total 300 units of insulin. You can set doses from 1 to 80 units in steps of 1 unit. The pen plunger moves with each dose. The plunger will only move to the end of the cartridge when 300 units of insulin have been given.

Keep this leaflet for future reference.

If you have any questions about SoloStar or about diabetes, ask your healthcare professional, go to www.winthropus.com or call sanofi-aventis at 1-800-633-1610.

Important information for use of SoloStar:

- Do not share your Insulin glargine SoloStar pen with other people, even if the needle has been changed. You may give other people a serious infection, or get a serious infection from them.
- Do not re-use needles. Always attach a new needle before each use.
- BD Ultra-Fine® needles [The brands listed are the registered trademarks of their respective owners and are not trademarks of sanofi-aventis U.S. LLC] are compatible with SoloStar. These are sold separately and are manufactured by BD. Contact your healthcare professional for further information.
- Always perform the safety test before each injection.
- Do not select a dose or press the injection button without a needle attached.
- If your injection is given by another person, special caution must be taken by this person to avoid accidental needle injury and transmission of infection.
- Never use SoloStar if it is damaged or if you are not sure that it is working properly.
- Always have a spare SoloStar in case your SoloStar is lost or damaged.
- Change (rotate) your injection sites within the area you choose for each dose (see "Places to inject").

Places to inject

- Inject your insulin exactly as your healthcare provider has shown you.
- Inject your insulin under the skin (subcutaneously) of your upper legs (thighs), upper arms, or stomach area (abdomen).
- Change (rotate) your injection sites within the area you choose for each dose to reduce your risk of getting lipodystrophy (pits in skin or thickened skin) and localized cutaneous amyloidosis (skin with lumps) at the injection sites.
- Do not inject where the skin has pits, is thickened, or has lumps.
- Do not inject where the skin is tender, bruised, scaly or hard, or into scars or damaged skin.

Step 1. Check the insulin

A. Check the label on your SoloStar to make sure you have the correct insulin. The Insulin glargine SoloStar is grey with a purple injection button.
B. Take off the pen cap.
C. Check the appearance of your insulin. Insulin glargine is a clear insulin. Do not use this SoloStar if the insulin is cloudy, colored or has particles.

Step 2. Attach the needle

Do not re-use needles. Always use a new sterile needle for each injection. This helps prevent contamination and potential needle blocks.

A. Wipe the Rubber Seal with alcohol.
B. Remove the protective seal from a new needle.
C. Line up the needle with the pen, and keep it straight as you attach it (screw or push on, depending on the needle type).
  - If the needle is not kept straight while you attach it, it can damage the rubber seal and cause leakage, or break the needle.

Step 3. Perform a Safety test

Always perform the safety test before each injection.

Performing the safety test ensures that you get an accurate dose by:

- ensuring that pen and needle work properly
- removing air bubbles

A. Select a dose of 2 units by turning the dosage selector.
B. Take off the outer needle cap and keep it to remove the used needle after injection. Take off the inner needle cap and discard it.
C. Hold the pen with the needle pointing upwards.
D. Tap the insulin reservoir so that any air bubbles rise up towards the needle.
E. Press the injection button all the way in. Check if insulin comes out of the needle tip.

You may have to perform the safety test several times before insulin is seen.

- If no insulin comes out, check for air bubbles and repeat the safety test two more times to remove them.
- If still no insulin comes out, the needle may be blocked. Change the needle and try again.
- If no insulin comes out after changing the needle, your SoloStar may be damaged. Do not use this SoloStar.

Step 4. Select the dose

You can set the dose in steps of 1 unit, from a minimum of 1 unit to a maximum of 80 units. If you need a dose greater than 80 units, you should give it as two or more injections.

A. Check that the dose window shows "0" following the safety test.
B. Select your required dose (in the example below, the selected dose is 30 units). If you turn past your dose, you can turn back down.
  - Do not push the injection button while turning, as insulin will come out.
  - You cannot turn the dosage selector past the number of units left in the pen. Do not force the dosage selector to turn. In this case, either you can inject what is remaining in the pen and complete your dose with a new SoloStar or use a new SoloStar for your full dose.

Step 5. Inject the dose

A. Use the injection method as instructed by your healthcare professional.
B. Insert the needle into the skin.
C. Deliver the dose by pressing the injection button in all the way. The number in the dose window will return to "0" as you inject.
D. Keep the injection button pressed all the way in.
  Slowly count to 10 before you withdraw the needle from the skin. This ensures that the full dose will be delivered.

Step 6. Remove and discard the needle

Always remove the needle after each injection and store SoloStar without a needle attached. This helps prevent:

- Contamination and/or infection.
- Entry of air into the insulin reservoir and leakage of insulin, which can cause inaccurate dosing.

A. Put the outer needle cap back on the needle, and use it to unscrew the needle from the pen. To reduce the risk of accidental needle injury, never replace the inner needle cap.
  - If your injection is given by another person, special caution must be taken by this person when removing and disposing the needle. Follow recommended safety measures for removal and disposal of needles (e.g., a one-handed capping technique) in order to reduce the risk of accidental needle injury and transmission of infectious diseases.
B. Dispose of the needle safely. Used needles should be placed in sharps containers (such as red biohazard containers), hard plastic containers (such as detergent bottles), or metal containers (such as an empty coffee can). Such containers should be sealed and disposed of properly.
  If you are giving an injection to another person, you should remove the needle in an approved manner to avoid needle-stick injuries.
C. Always put the pen cap back on the pen, then store the pen until your next injection.

Storage Instructions

Please check the leaflet for the insulin for complete instructions on how to store SoloStar.

If your SoloStar is in cool storage, take it out 1 to 2 hours before you inject to allow it to warm up. Cold insulin is more painful to inject.

Keep SoloStar out of the reach and sight of children.

Keep your SoloStar in cool storage (36°F–46°F [2°C–8°C]) until first use. Do not allow it to freeze. Do not put it next to the freezer compartment of your refrigerator or next to a freezer pack.

Once you take your SoloStar out of cool storage, for use or as a spare, you can use it for up to 28 days. During this time it can be safely kept at room temperature up to 86°F (30°C). Do not use it after this time. SoloStar in use must not be stored in a refrigerator.

Do not use SoloStar after the expiration date printed on the label of the pen or on the carton.

Protect SoloStar from light.

Discard your used SoloStar as required by your local authorities.

Maintenance

Protect your SoloStar from dust and dirt.

You can clean the outside of your SoloStar by wiping it with a damp cloth.

Do not soak, wash, or lubricate the pen as this may damage it.

Your SoloStar is designed to work accurately and safely. It should be handled with care. Avoid situations where SoloStar might be damaged. If you are concerned that your SoloStar may be damaged, use a new one.

This Instructions for Use has been approved by the U.S. Food and Drug Administration.

Revised: December 2020

Winthrop U.S.,
a business of sanofi-aventis U.S. LLC
Bridgewater, NJ 08807
A SANOFI COMPANY
©2020 sanofi-aventis U.S. LLC